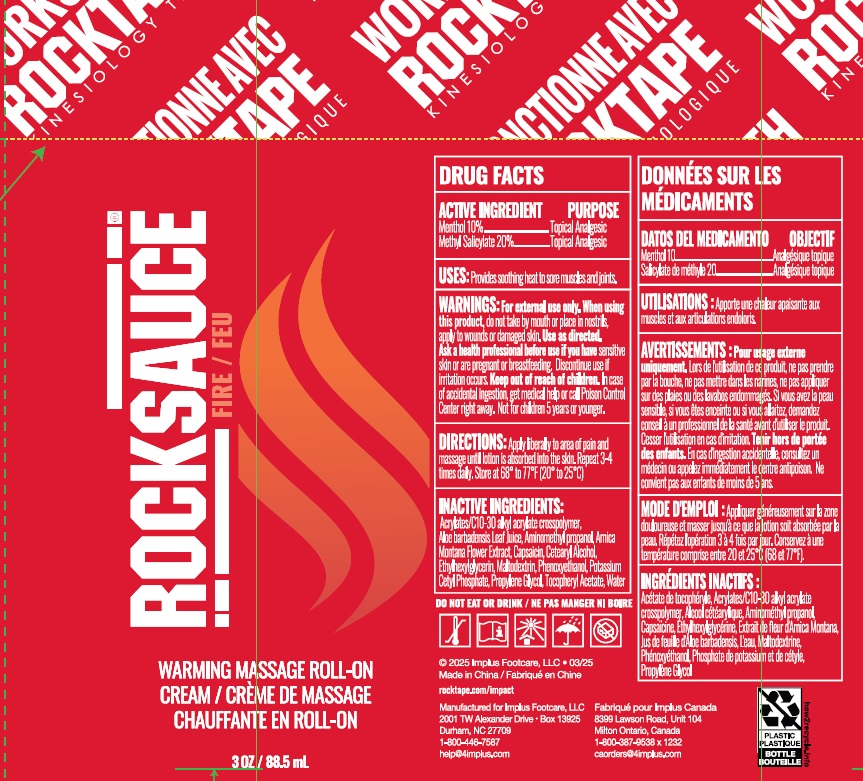 DRUG LABEL: RockSauce Warming Massage Roll On
NDC: 43473-077 | Form: CREAM
Manufacturer: Nantong Health & Beyond Hygienic Products Inc.
Category: otc | Type: HUMAN OTC DRUG LABEL
Date: 20250527

ACTIVE INGREDIENTS: MENTHOL 100 mg/1 mL; METHYL SALICYLATE 200 mg/1 mL
INACTIVE INGREDIENTS: ALOE VERA LEAF JUICE; ACRYLATES/C10-30 ALKYL ACRYLATE CROSSPOLYMER (60000 MPA.S AT 0.5%); AMINOMETHYL PROPANOL; ARNICA MONTANA FLOWER; CAPSAICIN; CETEARYL ALCOHOL; MALTODEXTRIN; PHENOXYETHANOL; POTASSIUM CETYL PHOSPHATE; PROPYLENE GLYCOL; ETHYLHEXYLGLYCERIN; .ALPHA.-TOCOPHEROL ACETATE; WATER

43473-077, RockSauce Warming Roll On

ACTIVE INGREDIENT

Menthol 10%

Methyl Salicylate 20%

PURPOSE

Topical Analgesic

USES:

Provides soothing heat to sore muscles and joints.

WARNINGS:

For external use only.

When using this product,

do not take by mouth or place in nostrils, apply to wounds or damaged skin. Use as directed.

Ask a health professional before use

if you have senstive skin or are pregnant or breastfeeding. Discontinue use if irritation occurs.

Keep out of reach of children.

In case of accidental ingestion, get medical help or call Poison Control Center right away. Not for children 5 years or youger.

DIRECTIONS:

Apply liberally to area of pain and massage until lotion is absorbed into the skin. Repeat 3-4 times daily. Store at 68°to 77°F (20° to 25°C)

INACTIVE INGREDIENTS:

ACRYLATES/C10-30 ALKYL ACRYLATE CROSSPOLYMER, ALOE BARBADENSIS LEAF JUICE, AMINOMETHYL PROPANOL, ARNICA MONTANA FLOWER EXTRACT, CAPSAICIN, CETEARYL ALCOHOL, MALTODEXTRIN, PHENOXYETHANOL, ETHYLHEXYLGLYCERIN, POTASSIUM CETYL PHOSPHATE, PROPYLENE GLYCOL, TOCOPHERYL ACETATE, WATER